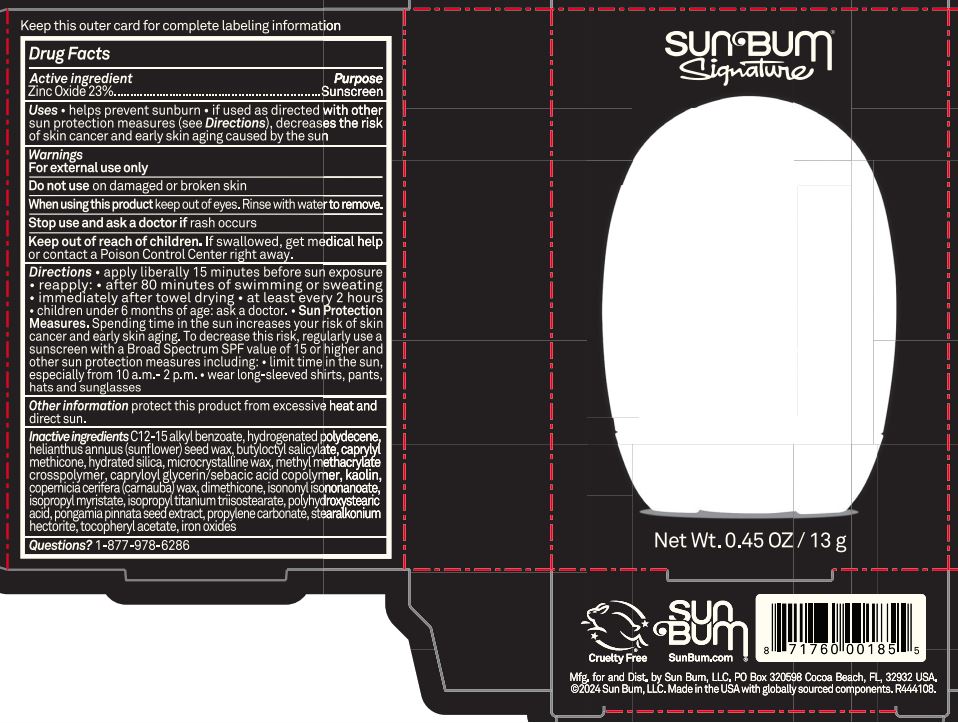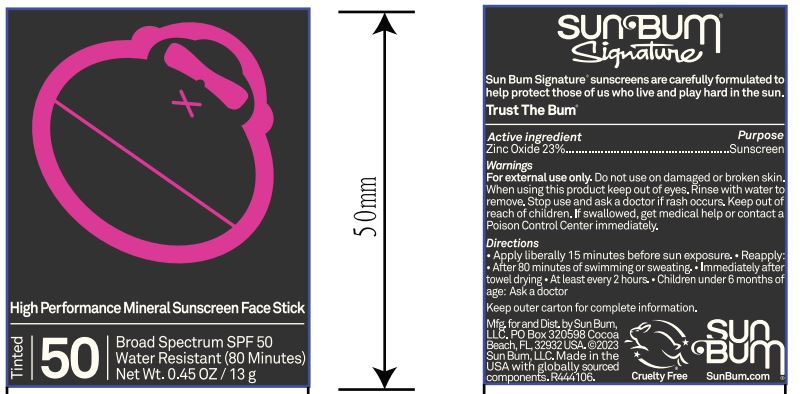 DRUG LABEL: Sun Bum Signature High Performance Mineral Sunscreen Face Stick Tinted 50
NDC: 69039-679 | Form: STICK
Manufacturer: Sun Bum, LLC
Category: otc | Type: HUMAN OTC DRUG LABEL
Date: 20250819

ACTIVE INGREDIENTS: ZINC OXIDE 230 mg/1 g
INACTIVE INGREDIENTS: POLY(METHYL METHACRYLATE; 450000 MW); BUTYLOCTYL SALICYLATE; PONGAMIA PINNATA SEED; DIMETHICONE; COPERNICIA CERIFERA (CARNAUBA) WAX; HYDRATED SILICA; HYDROGENATED POLYDECENE (1500 CST); ISOPROPYL MYRISTATE; CAPRYLYL METHICONE; ISOPROPYL TITANIUM TRIISOSTEARATE; FERRIC OXIDE RED; CAPRYLOYL GLYCERIN/SEBACIC ACID COPOLYMER (2000 MPA.S); POLYHYDROXYSTEARIC ACID (2300 MW); MICROCRYSTALLINE WAX; ISONONYL ISONONANOATE; .ALPHA.-TOCOPHEROL ACETATE; C12-15 ALKYL BENZOATE; KAOLIN; HELIANTHUS ANNUUS (SUNFLOWER) SEED WAX; PROPYLENE CARBONATE; STEARALKONIUM HECTORITE

Sun Bum Signature High Performance Mineral Sunscreen Face Stick Tinted 50

Active ingredients:

Zinc Oxide 23%

Purpose

Sunscreen

Uses

• helps prevent sunburn • if used as directed with other sun protection measures, (see Directions) decreases the risk of skin cancer and early skin aging caused by the sun

Warnings

For external use only

Do not use on damaged or broken skin

When using this product keep out of eyes. Rinse with water to remove.

Stop use and ask a doctor if rash occurs

Keep out of reach of children. If swallowed, get medical help or contact a Poison Control Center immediately.

Warnings

Keep Out Of Reach Of Children

Directions

• apply liberally 15 minutes before sun exposure

• reapply: • after 80 minutes of swimming or sweating • immediately after towel drying • at least every 2 hours

• children under 6 months of age: ask a doctor

• Sun Protection Measures. Spending time in the sun increases your risk of skin cancer and early skin aging. To decrease this risk, regularly use a sunscreen with a Broad Spectrum SPF value of 15 or higher and other sun protection measures including:

• limit time in the sun, especially from 10 a.m.- 2 p.m.

• wear long-sleeved shirts, pants, hats and sunglasses

Directions

• apply liberally 15 minutes before sun exposure

Other information

protect this product from excessive heat and direct sun

Inactive ingredients

C12-15 alkyl benzoate, hydrogenated polydecene, helianthus annuus (sunﬂower) seed wax, butyloctyl salicylate, caprylyl methicone, hydrated silica, microcrystalline wax, methyl methacrylate crosspolymer, capryloyl glycerin/sebacic acid copolymer, kaolin, copernicia cerifera (carnauba) wax, dimethicone, isononylisononanoate,isopropyl myristate, isopropyl titanium triisostearate,polyhydroxystearicacid, pongamia pinnata seed extract, propylene carbonate, stearalkoniumhectorite, tocopheryl acetate, iron oxides

Questions?

1-877-978-6286